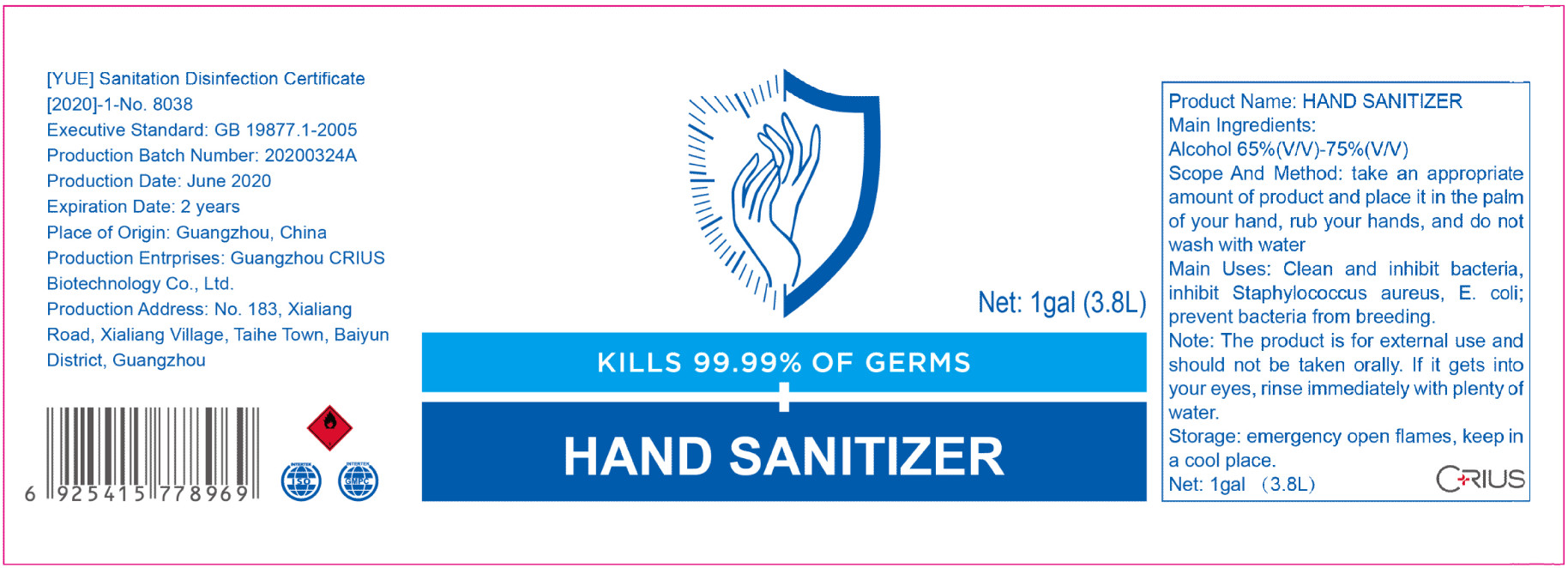 DRUG LABEL: Hand sanitizer
NDC: 54158-003 | Form: GEL
Manufacturer: Guangzhou CRIUS Biotechnology Co., Ltd.
Category: otc | Type: HUMAN OTC DRUG LABEL
Date: 20200702

ACTIVE INGREDIENTS: ALCOHOL 2660 mL/3800 mL
INACTIVE INGREDIENTS: CARBOMER HOMOPOLYMER, UNSPECIFIED TYPE; AMINOMETHYLPROPANOL; WATER; GLYCERIN

DOSAGE AND ADMINISTRATION

keep in a cool place.

INACTIVE INGREDIENT

Water

Glycerol

Carbomer

AMINOMETHYL PROPANOL

INDICATIONS AND USAGE

take an appropriate amount of product and place it in the palm of your hand,rub your hands, and do not wash with water

ACTIVE INGREDIENT

Ethanol

keep out of reach of children

PURPOSE

Disinfection
Sterilization
No Rinseing

WARNINGS

The product is for external use and should not be taken orally. If it gets into your eyes, rinse immediately with plenty of water.